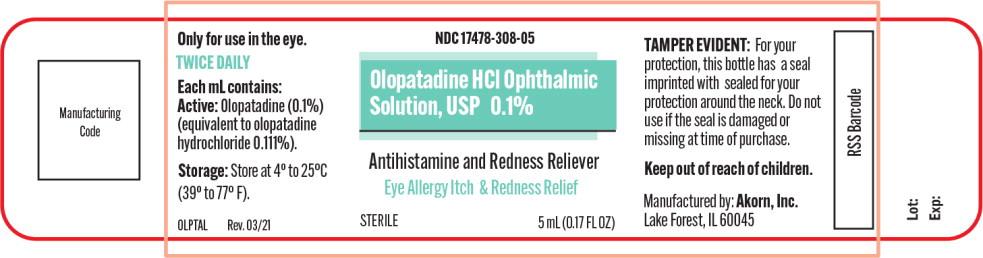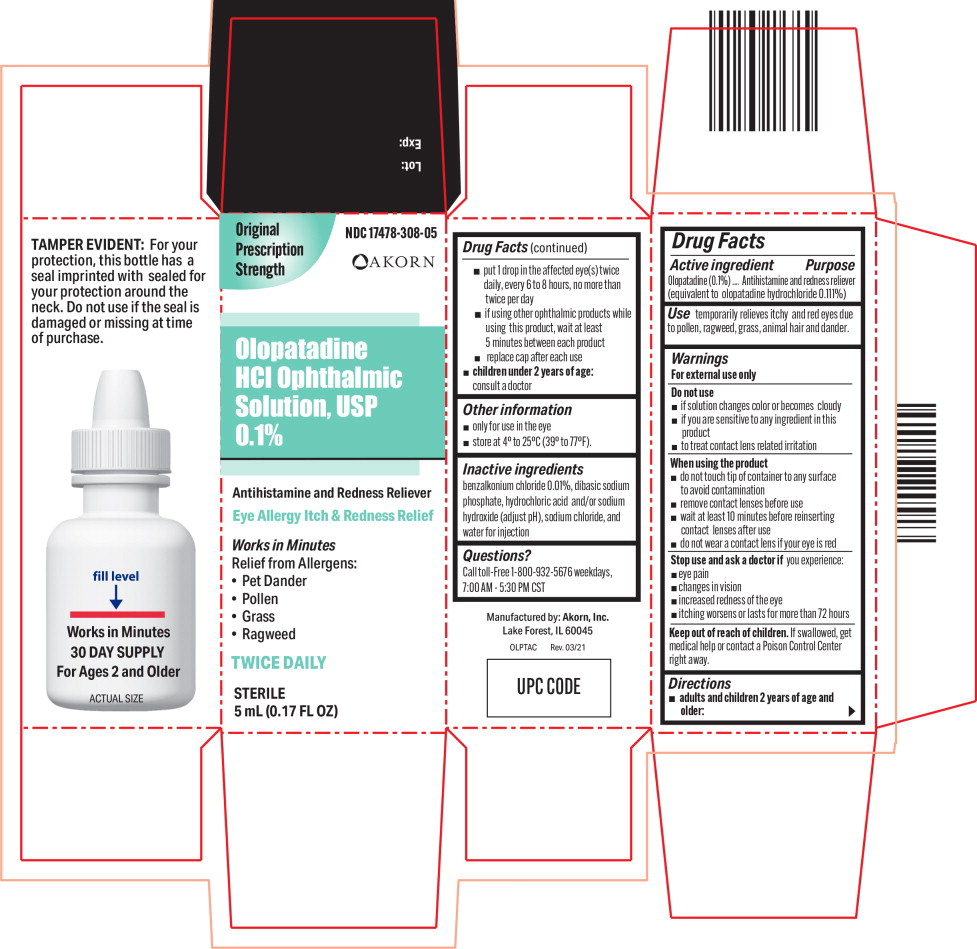 DRUG LABEL: Olopatadine
NDC: 17478-308 | Form: SOLUTION/ DROPS
Manufacturer: Akorn
Category: otc | Type: HUMAN OTC DRUG LABEL
Date: 20220203

ACTIVE INGREDIENTS: Olopatadine Hydrochloride 1 mg/1 mL
INACTIVE INGREDIENTS: benzalkonium chloride; sodium phosphate, dibasic, unspecified form; hydrochloric acid; sodium hydroxide; sodium chloride; water

Drug Facts

Active ingredient

Olopatadine (0.1%)

(equivalent to olopatadine hydrochloride 0.111%)

Purpose

Antihistamine and redness reliever

Use

temporarily relieves itchy and red eyes due to pollen, ragweed, grass, animal hair and dander.

Warnings

For external use only

Do not use

- if solution changes color or becomes cloudy
- if you are sensitive to any ingredient in this product
- to treat contact lens related irritation

When using the product

- do not touch tip of container to any surface to avoid contamination
- remove contact lenses before use
- wait at least 10 minutes before reinserting contact lenses after use
- do not wear a contact lens if your eye is red

Stop use and ask a doctor if you experience:

- eye pain
- changes in vision
- increased redness of the eye
- itching worsens or lasts for more than 72 hours

Keep out of reach of children. If swallowed, get medical help or contact a Poison Control Center right away.

Directions

- adults and children 2 years of age and older:
  - put 1 drop in the affected eye(s) twice daily, every 6 to 8 hours, no more than twice per day
  - if using other ophthalmic products while using this product, wait at least 5 minutes between each product
  - replace cap after each use
- children under 2 years of age: consult a doctor

Other information

- only for use in the eye
- store at 4° to 25°C (39° to 77°F).

Inactive ingredients

benzalkonium chloride 0.01%, dibasic sodium phosphate, hydrochloric acid and/or sodium hydroxide (adjust pH), sodium chloride, and water for injection

Questions?

Call toll-Free 1-800-932-5676 weekdays, 7:00 AM - 5:30 PM CST

Principal Display Panel Text for Container Label:

NDC 17478-308-05

Olopatadine HCl Ophthalmic

Solution, USP 0.1%

Antihistamine and Redness Reliever

Eye Allergy Itch & Redness Relief

STERILE 5 mL (0.17 FL OZ)

Principal Display Panel Text for Carton Label:

Original NDC 17478-308-05

Prescription

Strength Akorn logo

Olopatadine

HCl Ophthalmic

Solution, USP

0.1%

Antihistamine and Redness Reliever

Eye Allergy Itch & Redness Relief

Works in Minutes

Relief from Allergens:

• Pet Dander

• Pollen

• Grass

• Ragweed

TWICE DAILY

STERILE

5 mL (0.17 FL OZ)